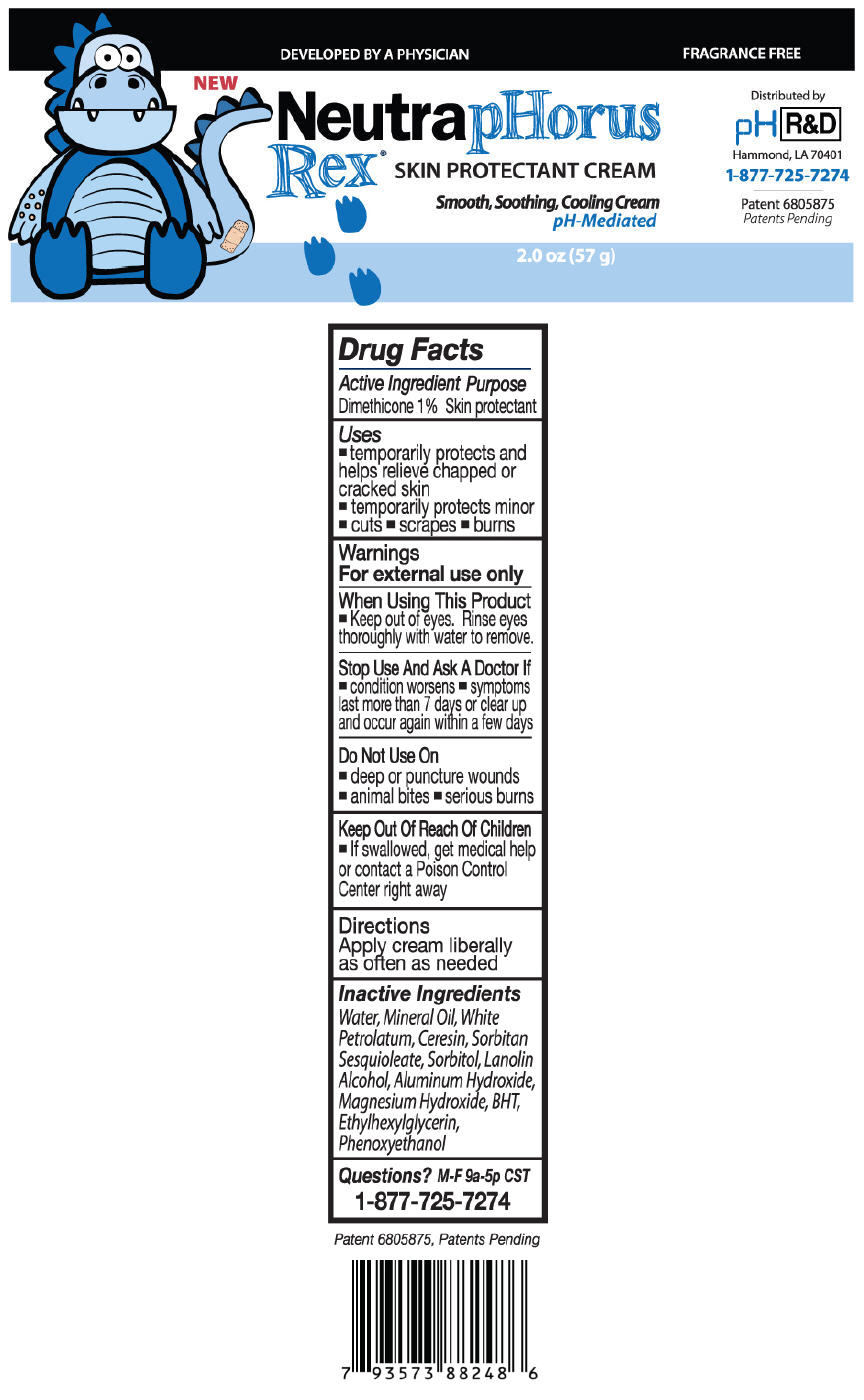 DRUG LABEL: NeutrapHorus Rex
NDC: 50952-003 | Form: CREAM
Manufacturer: pH R&D LLC
Category: otc | Type: HUMAN OTC DRUG LABEL
Date: 20121113

ACTIVE INGREDIENTS: Dimethicone 0.57 g/57 g
INACTIVE INGREDIENTS: Water; Mineral Oil; Petrolatum; Ceresin; Sorbitan Sesquioleate; Sorbitol; Lanolin Alcohols; Aluminum Hydroxide; Magnesium Hydroxide; Butylated Hydroxytoluene; Ethylhexylglycerin; Phenoxyethanol

NeutrapHorus
Rex® SKIN PROTECTANT CREAM

Drug Facts

Active Ingredient

Dimethicone 1%

Purpose

Skin protectant

Uses

- temporarily protects and helps relieve chapped or cracked skin
- temporarily protects minor
- cuts
- scrapes
- burns

Warnings

For external use only

When Using This Product

- Keep out of eyes. Rinse eyes thoroughly with water to remove.

Stop Use And Ask A Doctor If

- condition worsens
- symptoms last more than 7 days or clear up and occur again within a few days

Do Not Use On

- deep or puncture wounds
- animal bites
- serious burns

Keep Out Of Reach Of Children

- If swallowed, get medical help or contact a Poison Control Center right away

Directions

Apply cream liberally as often as needed

Inactive Ingredients

Water, Mineral Oil, White Petrolatum, Ceresin, Sorbitan Sesquioleate, Sorbitol, Lanolin Alcohol, Aluminum Hydroxide, Magnesium Hydroxide, BHT, Ethylhexylglycerin, Phenoxyethanol

Questions?

M-F 9a-5p CST

1-877-725-7274

PRINCIPAL DISPLAY PANEL - 57 g Jar

DEVELOPED BY A PHYSICIAN

FRAGRANCE FREE

NEW

NeutrapHorus
Rex® SKIN PROTECTANT CREAM

Smooth, Soothing, Cooling Cream
pH-Mediated

2.0 oz (57 g)

Distributed by
pH R&D
Hammond, LA 70401

1-877-725-7274

Patent 6805875
Patents Pending